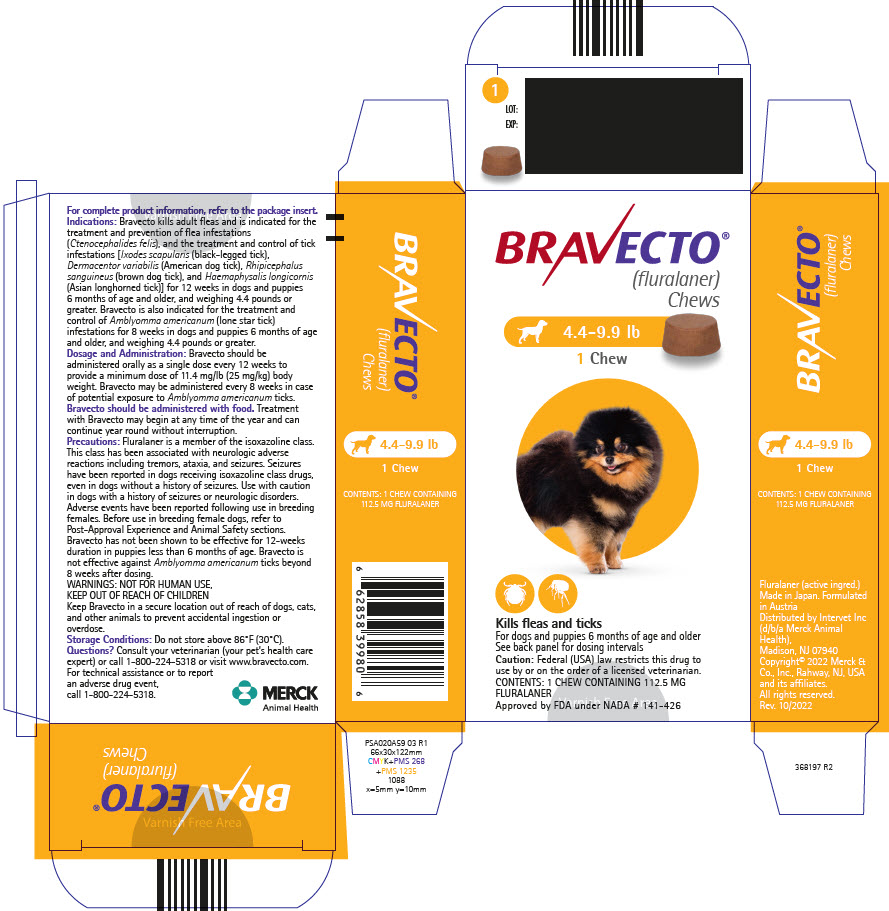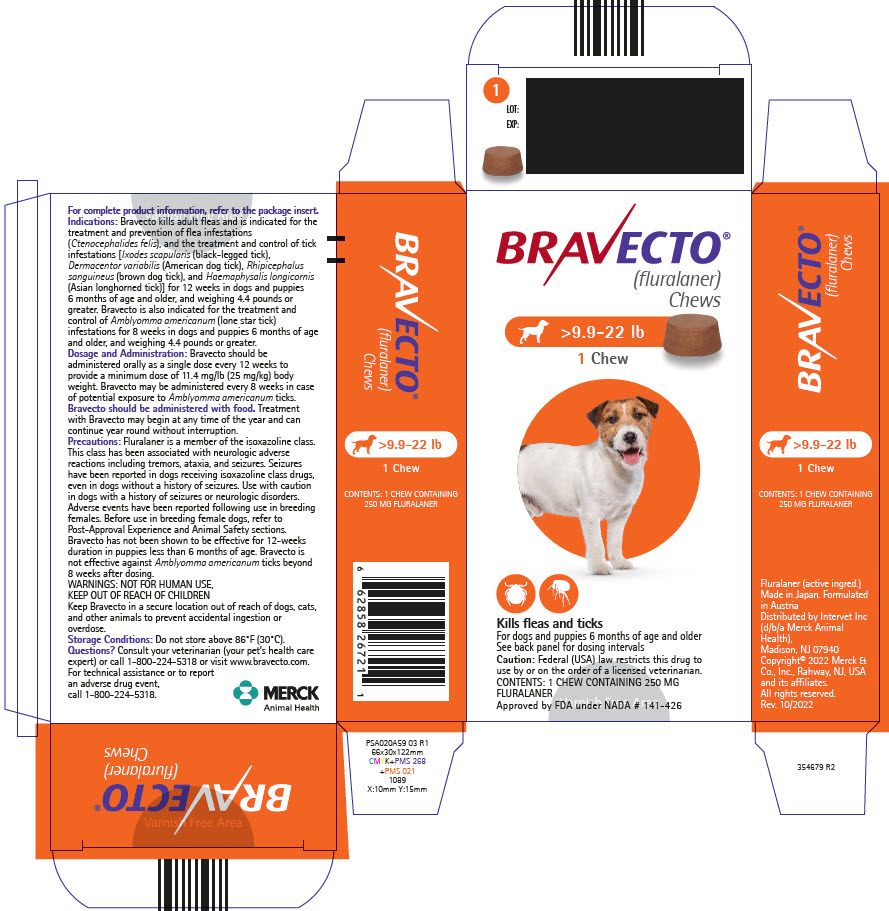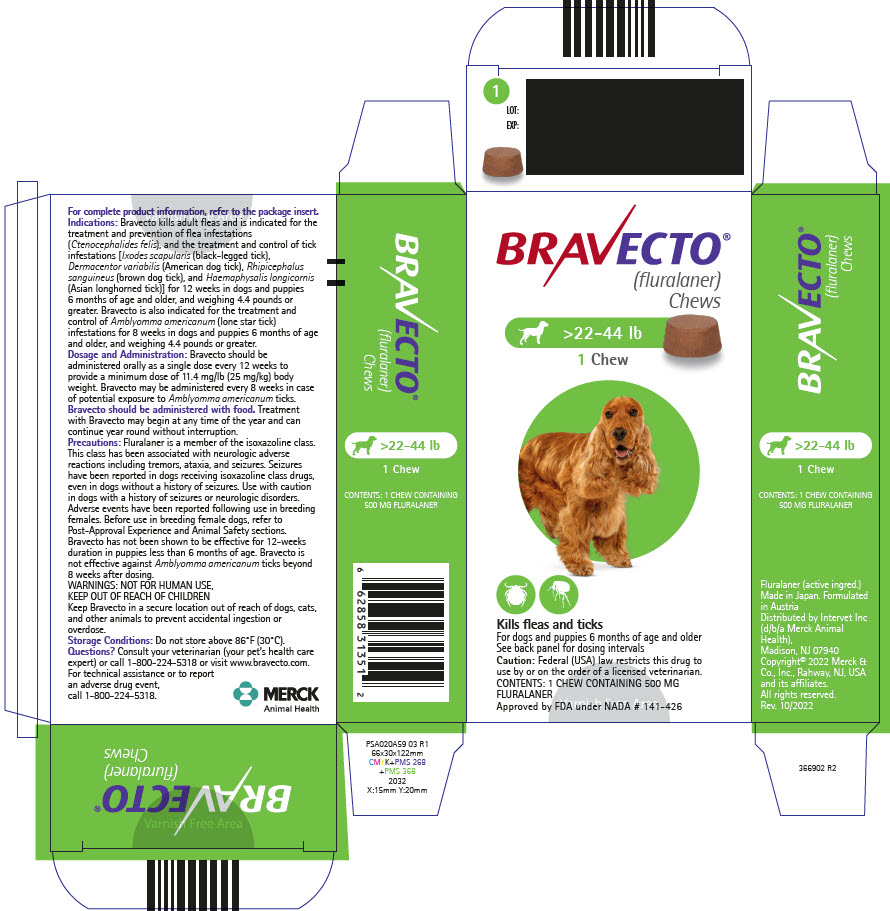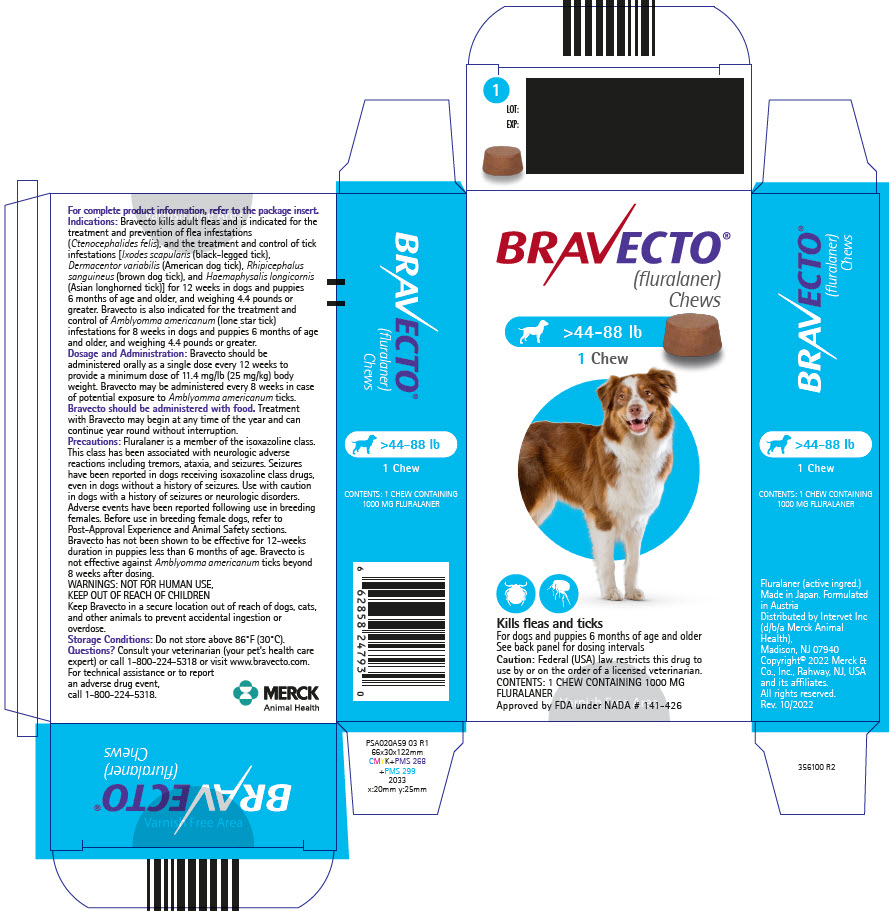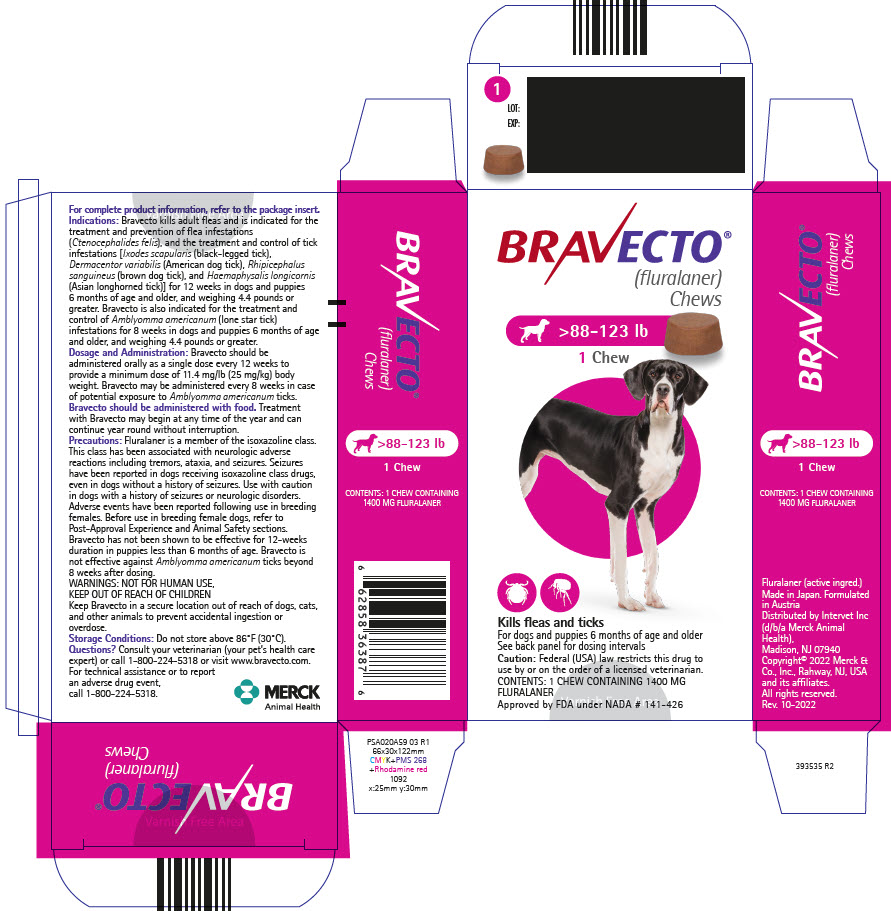 DRUG LABEL: Bravecto
NDC: 0061-4340 | Form: TABLET, CHEWABLE
Manufacturer: Merck Sharp & Dohme Corp.
Category: animal | Type: PRESCRIPTION ANIMAL DRUG LABEL
Date: 20241029

ACTIVE INGREDIENTS: FLURALANER 112.5 mg/1 1

BRAVECTO® (fluralaner) Chews

Flavored chews for dogs.

Caution:

Federal (USA) law restricts this drug to use by or on the order of a licensed veterinarian.

Description:

Each chew is formulated to provide a minimum dose of 11.4 mg/lb (25 mg/kg) body weight.

The chemical name of fluralaner is (±)-4-[5-(3,5-dichlorophenyl)-5-(trifluoromethyl)-4,5-dihydroisoxazol-3-yl]-2-methyl-N-[2-oxo-2-(2,2,2-trifluoroethylamino) ethyl]benzamide.

Indications:

Bravecto kills adult fleas and is indicated for the treatment and prevention of flea infestations (Ctenocephalides felis), and the treatment and control of tick infestations [Ixodes scapularis (black-legged tick), Dermacentor variabilis (American dog tick), Rhipicephalus sanguineus (brown dog tick), and Haemaphysalis longicornis (Asian longhorned tick)] for 12 weeks in dogs and puppies 6 months of age and older, and weighing 4.4 pounds or greater.

Bravecto is also indicated for the treatment and control of Amblyomma americanum (lone star tick) infestations for 8 weeks in dogs and puppies 6 months of age and older, and weighing 4.4 pounds or greater.

Dosage and Administration:

Bravecto should be administered orally as a single dose every 12 weeks according to the Dosage Schedule below to provide a minimum dose of 11.4 mg/lb (25 mg/kg) body weight.

Bravecto may be administered every 8 weeks in case of potential exposure to Amblyomma americanum ticks (see Effectiveness).

Bravecto should be administered with food.

Dosage Schedule
Body Weight Ranges (lb) | Fluralaner Content (mg) | Chews Administered
4.4 – 9.9 | 112.5 | One
>9.9 – 22.0 | 250 | One
>22.0 – 44.0 | 500 | One
>44.0 – 88.0 | 1000 | One
>88.0 – 123.0 [Dogs over 123.0 lb should be administered the appropriate combination of chews] | 1400 | One

Treatment with Bravecto may begin at any time of the year and can continue year round without interruption.

Contraindications:

There are no known contraindications for the use of the product.

Warnings:

Not for human use. Keep this and all drugs out of the reach of children. Keep the product in the original packaging until use, in order to prevent children from getting direct access to the product. Do not eat, drink or smoke while handling the product. Wash hands thoroughly with soap and water immediately after use of the product.

Keep Bravecto in a secure location out of reach of dogs, cats, and other animals to prevent accidental ingestion or overdose.

Precautions:

Fluralaner is a member of the isoxazoline class. This class has been associated with neurologic adverse reactions including tremors, ataxia, and seizures. Seizures have been reported in dogs receiving isoxazoline class drugs, even in dogs without a history of seizures. Use with caution in dogs with a history of seizures or neurologic disorders.

Adverse events have been reported following use in breeding females. Before use in breeding female dogs, refer to Post-Approval Experience and Animal Safety sections.

Bravecto has not been shown to be effective for 12-weeks duration in puppies less than 6 months of age. Bravecto is not effective against Amblyomma americanum ticks beyond 8 weeks after dosing (see Effectiveness).

Adverse Reactions:

In a well-controlled U.S. field study, which included 294 dogs (224 dogs were administered Bravecto every 12 weeks and 70 dogs were administered an oral active control every 4 weeks and were provided with a tick collar); there were no serious adverse reactions. All potential adverse reactions were recorded in dogs treated with Bravecto over a 182-day period and in dogs treated with the active control over an 84-day period. The most frequently reported adverse reaction in dogs in the Bravecto and active control groups was vomiting.

Percentage of Dogs with Adverse Reactions in the Field Study
Adverse Reaction (AR) | Bravecto Group: Percentage of Dogs with the AR During the 182-Day Study (n=224 dogs) | Active Control Group: Percentage of Dogs with the AR During the 84-Day Study (n=70 dogs)
Vomiting | 7.1 | 14.3
Decreased Appetite | 6.7 | 0.0
Diarrhea | 4.9 | 2.9
Lethargy | 5.4 | 7.1
Polydipsia | 1.8 | 4.3
Flatulence | 1.3 | 0.0

In a well-controlled laboratory dose confirmation study, one dog developed edema and hyperemia of the upper lips within one hour of receiving Bravecto. The edema improved progressively through the day and had resolved without medical intervention by the next morning.

Post-Approval Experience (2022):

The following adverse events are based on post-approval adverse drug experience reporting for fluralaner. Not all adverse events are reported to FDA/CVM. It is not always possible to reliably estimate the adverse event frequency or establish a causal relationship to product exposure using these data.

The following adverse events reported for dogs are listed in decreasing order of reporting frequency:

Vomiting, lethargy, diarrhea (with and without blood), anorexia, pruritis, polydipsia, seizure, allergic reactions (including hives, swelling, erythema), dermatitis (including crusts, pustules, rash), tremors and ataxia. In some cases, birth defects (including limb deformities and cleft palate), stillbirth, and abortion have been reported after treatment of breeding females.

Contact Information:

To report suspected adverse events, for technical assistance or to obtain a copy of the Safety Data Sheet (SDS), contact Merck Animal Health at 1-800-224-5318. Additional information can be found at www.bravecto.com.

For additional information about adverse drug experience reporting for animal drugs, contact FDA at 1-888-FDA-VETS or online at http://www.FDA.gov/reportanimalae.

Clinical Pharmacology:

Peak fluralaner concentrations are achieved between 2 hours and 3 days following oral administration, and the elimination half-life ranges between 9.3 to 16.2 days. Quantifiable drug concentrations can be measured (lower than necessary for effectiveness) through 112 days. Due to reduced drug bioavailability in the fasted state, fluralaner should be administered with food.

Mode of Action:

Fluralaner is for systemic use and belongs to the class of isoxazoline-substituted benzamide derivatives. Fluralaner is an inhibitor of the arthropod nervous system. The mode of action of fluralaner is the antagonism of the ligand-gated chloride channels (gamma-aminobutyric acid (GABA)-receptor and glutamate-receptor).

Effectiveness:

Bravecto began to kill fleas within two hours after administration in a well-controlled laboratory study. In a European laboratory study, Bravecto killed fleas and Ixodes ricinus ticks and reduced the numbers of live fleas and Ixodes ricinus ticks on dogs by > 98% within 12 hours for 12 weeks. In a well-controlled laboratory study, Bravecto demonstrated 100% effectiveness against adult fleas 48 hours post-infestation for 12 weeks. In well-controlled laboratory studies, Bravecto demonstrated ≥ 93% effectiveness against Dermacentor variabilis, Ixodes scapularis, Rhipicephalus sanguineus, and Haemaphysalis longicornis ticks 48 hours post-infestation for 12 weeks. Bravecto demonstrated ≥90% effectiveness against Amblyomma americanum 72 hours post-infestation for 8 weeks, but failed to demonstrate ≥90% effectiveness beyond 8 weeks.

In a well-controlled U.S. field study, a single dose of Bravecto reduced fleas by ≥ 99.7% for 12 weeks. Dogs with signs of flea allergy dermatitis showed improvement in erythema, alopecia, papules, scales, crusts, and excoriation as a direct result of eliminating flea infestations.

Palatability: In a well-controlled U.S. field study, which included 559 doses administered to 224 dogs, 80.7% of dogs voluntarily consumed Bravecto within 5 minutes, an additional 12.5% voluntarily consumed Bravecto within 5 minutes when offered with food, and 6.8% refused the dose or required forced administration.

Animal Safety:

Margin of Safety Study: In a margin of safety study, Bravecto was administered orally to 8- to 9-week-old puppies at 1, 3, and 5× the maximum label dose of 56 mg/kg at three, 8-week intervals. The dogs in the control group (0×) were untreated.

There were no clinically-relevant, treatment-related effects on physical examinations, body weights, food consumption, clinical pathology (hematology, clinical chemistries, coagulation tests, and urinalysis), gross pathology, histopathology, or organ weights. Diarrhea, mucoid and bloody feces were the most common observations in this study, occurring at a similar incidence in the treated and control groups. Five of the twelve treated dogs that experienced one or more of these signs did so within 6 hours of the first dosing. One dog in the 3× treatment group was observed to be dull, inappetant, with evidence of bloody diarrhea, vomiting, and weight loss beginning five days after the first treatment. One dog in the 1× treatment group vomited food 4 hours following the first treatment.

Reproductive Safety Study: Bravecto was administered orally to intact, reproductively- sound male and female Beagles at a dose of up to 168 mg/kg (equivalent to 3× the maximum label dose) on three to four occasions at 8-week intervals. The dogs in the control group (0×) were untreated.

There were no clinically-relevant, treatment-related effects on the body weights, food consumption, reproductive performance, semen analysis, litter data, gross necropsy (adult dogs) or histopathology findings (adult dogs and puppies). One adult 3× treated dog suffered a seizure during the course of the study (46 days after the third treatment). Abnormal salivation was observed on 17 occasions: in six treated dogs (11 occasions) after dosing and four control dogs (6 occasions).

The following abnormalities were noted in 7 pups from 2 of the 10 dams in only the treated group during gross necropsy examination: limb deformity (4 pups), enlarged heart (2 pups), enlarged spleen (3 pups), and cleft palate (2 pups). During veterinary examination at Week 7, two pups from the control group had inguinal testicles, and two and four pups from the treated group had inguinal and cryptorchid testicles, respectively. No undescended testicles were observed at the time of necropsy (days 50 to 71).

In a well-controlled field study Bravecto (fluralaner) was used concurrently with other medications, such as vaccines, anthelmintics, antibiotics, and steroids. No adverse reactions were observed from the concurrent use of Bravecto with other medications.

Storage Information:

Do not store above 86°F (30°C).

How Supplied:

Bravecto is available in five strengths (112.5, 250, 500, 1000, and 1400 mg fluralaner per chew). Each chew is packaged individually into aluminum foil blister packs sealed with a peelable paper backed foil lid stock. Product may be packaged in 1, 2, or 4 chews per package.

Approved by FDA under NADA # 141-426

Distributed by:
Intervet Inc (d/b/a Merck Animal Health)
Madison, NJ 07940

Fluralaner (active ingred.) Made in Japan.
Formulated in Austria

Copyright © 2022 Merck & Co., Inc., Rahway, NJ, USA and its affiliates.
All rights reserved

Rev. 10/2022

375232 R4

PRINCIPAL DISPLAY PANEL - 112.5 MG Chew Blister Pack Carton

BRAVECTO®
(fluralaner)
Chews

4.4-9.9 lb

1 Chew

Kills fleas and ticks

For dogs and puppies 6 months of age and older
See back panel for dosing intervals
Caution: Federal (USA) law restricts this drug to
use by or on the order of a licensed veterinarian.
CONTENTS: 1 CHEW CONTAINING 112.5 MG
FLURALANER
Approved by FDA under NADA # 141-426

PRINCIPAL DISPLAY PANEL - 250 MG Chew Blister Pack Carton

BRAVECTO®
(fluralaner)
Chews

>9.9-22 lb

1 Chew

Kills fleas and ticks

For dogs and puppies 6 months of age and older
See back panel for dosing intervals
Caution: Federal (USA) law restricts this drug to
use by or on the order of a licensed veterinarian.
CONTENTS: 1 CHEW CONTAINING 250 MG
FLURALANER
Approved by FDA under NADA # 141-426

PRINCIPAL DISPLAY PANEL - 500 MG Chew Blister Pack Carton

BRAVECTO®
(fluralaner)
Chews

>22-44 lb

1 Chew

Kills fleas and ticks

For dogs and puppies 6 months of age and older
See back panel for dosing intervals
Caution: Federal (USA) law restricts this drug to
use by or on the order of a licensed veterinarian.
CONTENTS: 1 CHEW CONTAINING 500 MG
FLURALANER
Approved by FDA under NADA # 141-426

PRINCIPAL DISPLAY PANEL - 1000 MG Chew Blister Pack Carton

BRAVECTO®
(fluralaner)
Chews

>44-88 lb

1 Chew

Kills fleas and ticks

For dogs and puppies 6 months of age and older
See back panel for dosing intervals
Caution: Federal (USA) law restricts this drug to
use by or on the order of a licensed veterinarian.
CONTENTS: 1 CHEW CONTAINING 1000 MG
FLURALANER
Approved by FDA under NADA # 141-426

PRINCIPAL DISPLAY PANEL - 1400 MG Chew Blister Pack Carton

BRAVECTO®
(fluralaner)
Chews

>88-123 lb

1 Chew

Kills fleas and ticks

For dogs and puppies 6 months of age and older
See back panel for dosing intervals
Caution: Federal (USA) law restricts this drug to
use by or on the order of a licensed veterinarian.
CONTENTS: 1 CHEW CONTAINING 1400 MG
FLURALANER
Approved by FDA under NADA # 141-426